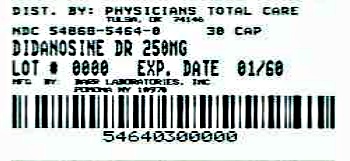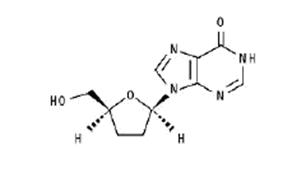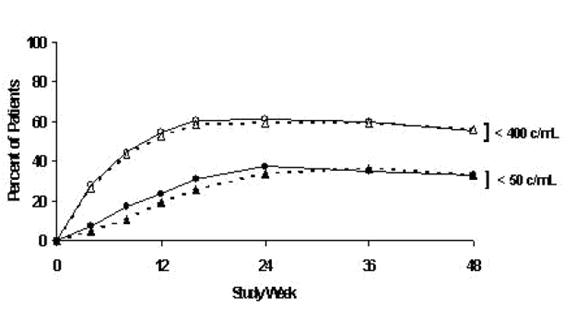 DRUG LABEL: Didanosine
NDC: 54868-5464 | Form: CAPSULE, DELAYED RELEASE PELLETS
Manufacturer: Physicians Total Care, Inc.
Category: prescription | Type: HUMAN PRESCRIPTION DRUG LABEL
Date: 20120502

ACTIVE INGREDIENTS: DIDANOSINE 250 mg/1 1
INACTIVE INGREDIENTS: FERROSOFERRIC OXIDE; CROSCARMELLOSE SODIUM; D&C YELLOW NO. 10; ALUMINUM OXIDE; FD&C BLUE NO. 1; FD&C BLUE NO. 2; FD&C RED NO. 40; GELATIN; HYDROXYPROPYL CELLULOSE; HYPROMELLOSES; METHACRYLIC ACID; CELLULOSE, MICROCRYSTALLINE; POLYDEXTROSE; POLYETHYLENE GLYCOL; PROPYLENE GLYCOL; SHELLAC; SILICON DIOXIDE; SODIUM HYDROXIDE; TALC; TITANIUM DIOXIDE; TRIACETIN; TRIETHYL CITRATE; D&C RED NO. 28

HIGHLIGHTS OF PRESCRIBING INFORMATION

These highlights do not include all the information needed to use didanosine delayed-release capsules safely and effectively. See full prescribing information for didanosine delayed-release capsules.
Initial U.S. Approval: 1991

RECENT MAJOR CHANGES

Warnings and Precautions,

Immune Reconstitution Syndrome (5.7) 11/2011

WARNING: PANCREATITIS, LACTIC ACIDOSIS and HEPATOMEGALY with STEATOSIS

See full prescribing information for complete boxed warning.

- Fatal and nonfatal pancreatitis. Didanosine delayed-release capsules should be suspended in patients with suspected pancreatitis and discontinued in patients with confirmed pancreatitis.(5.1)
- Lactic acidosis and severe hepatomegaly with steatosis, including fatal cases. Fatal lactic acidosis has been reported in pregnant women who received the combination of didanosine and stavudine. (5.2)

1 INDICATIONS AND USAGE

Didanosine delayed-release capsules are a nucleoside reverse transcriptase inhibitor for use in combination with other antiretroviral agents for the treatment of human immunodeficiency virus (HIV)-1 infection. (1)

2 DOSAGE AND ADMINISTRATION

- Adult patients: Administered on an empty stomach. Dosing is based on body weight. (2.1)
- Pediatric patients: Ages 6 to 18 years, can safely swallow capsules and body weight at least 20 kg. Administered on an empty stomach, dosing is based on body weight. (2.1)

Body Weight | Dose
20 kg to less than 25 kg | 200 mg once daily
25 kg to less than 60 kg | 250 mg once daily
at least 60 kg | 400 mg once daily

- Renal impairment: Dose reduction is recommended. (2.2)
- Coadministration with tenofovir: Dose reduction is recommended. Patients should be monitored closely for didanosine-associated adverse reactions. (2.3, 7.1)

3 DOSAGE FORMS AND STRENGTHS

Capsules: 200 mg, 250 mg, 400 mg (3)

4 CONTRAINDICATIONS

Coadministration with allopurinol or ribavirin is contraindicated. (4.1 and 4.2)

5 WARNINGS AND PRECAUTIONS

- Pancreatitis: Suspension or discontinuation of didanosine may be necessary. (5.1)
- Lactic acidosis and severe hepatomegaly with steatosis: Suspend didanosine in patients who develop clinical symptoms or signs with or without laboratory findings. (5.2)
- Hepatic toxicity: Interruption or discontinuation of didanosine must be considered upon worsening of liver disease. (5.3)
- Non-cirrhotic portal hypertension: Discontinue didanosine in patients with evidence of non-cirrhotic portal hypertension. (5.4)
- Patients may develop peripheral neuropathy (5.5), retinal changes and optic neuritis (5.6), immune reconstitution syndrome (5.7), and redistribution/accumulation of body fat (5.8)

6 ADVERSE REACTIONS

- In adults, the most common adverse reactions (greater than 10%, all grades) are diarrhea, peripheral neurologic symptoms/neuropathy, nausea, headache, rash and vomiting. (6.1)
- Adverse reactions in pediatric patients were consistent with those in adults. (6.1)

To report SUSPECTED ADVERSE REACTIONS, contact TEVA USA, PHARMACOVIGILANCE at tel: 1-888-838-2872, X6351 or drug.safety@tevapharm.com; or FDA at 1-800-FDA-1088 or www.fda.gov/medwatch

7 DRUG INTERACTIONS

Coadministration of didanosine delayed-release capsules can alter the concentration of other drugs and other drugs may alter the concentration of didanosine. The potential drug-drug interactions must be considered prior to and during therapy. (4, 7, 12.3)

8 USE IN SPECIFIC POPULATIONS

Pregnancy: Fatal lactic acidosis has been reported in pregnant women who received both didanosine and stavudine with other agents. This combination should be used with caution during pregnancy and only if the potential benefit clearly outweighs the potential risk. (5.2, 8.1) Physicians are encouraged to register patients in the Antiretroviral Pregnancy Registry by calling 1-800-258-4263.

FULL PRESCRIBING INFORMATION

WARNING: PANCREATITIS, LACTIC ACIDOSIS and HEPATOMEGALY with STEATOSIS

Fatal and nonfatal pancreatitis has occurred during therapy with didanosine used alone or in combination regimens in both treatment-naive and treatment-experienced patients, regardless of degree of immunosuppression. Didanosine delayed-release capsules should be suspended in patients with suspected pancreatitis and discontinued in patients with confirmed pancreatitis [see Warnings and Precautions (5.1)].

Lactic acidosis and severe hepatomegaly with steatosis, including fatal cases, have been reported with the use of nucleoside analogues alone or in combination, including didanosine and other antiretrovirals. Fatal lactic acidosis has been reported in pregnant women who received the combination of didanosine and stavudine with other antiretroviral agents. The combination of didanosine and stavudine should be used with caution during pregnancy and is recommended only if the potential benefit clearly outweighs the potential risk [see Warnings and Precautions (5.2)].

1 INDICATIONS AND USAGE

Didanosine delayed-release capsules, also known as ddI, in combination with other antiretroviral agents is indicated for the treatment of human immunodeficiency virus (HIV)-1 infection [see Clinical Studies (14)].

2 DOSAGE AND ADMINISTRATION

Didanosine delayed-release capsules should be administered on an empty stomach. Didanosine delayed-release capsules should be swallowed intact.

2.1 Recommended Dosage (Adult and Pediatric Patients)

The recommended total daily dose is based on body weight and is administered as one capsule given on a once-daily schedule as outlined in Table 1.

The recommended total daily dose to be administered once daily to pediatric patients weighing at least 20 kg who can swallow capsules is based on body weight (kg), consistent with the recommended adult dosing guidelines (see Table 1). Please consult the complete prescribing information for Didanosine Pediatric Powder for Oral Solution for dosage and administration of didanosine to pediatric patients weighing less than 20 kg or who can not swallow capsules.

Table 1: Recommended Dosage (Adult and Pediatric Patients)
Body Weight | Dose
20 kg to less than 25 kg | 200 mg once daily
25 kg to less than 60 kg | 250 mg once daily
at least 60 kg | 400 mg once daily

2.2 Renal Impairment

Dosing recommendations for didanosine delayed-release capsules are different for patients with renal impairment.

Adult Patients

In adult patients with impaired renal function, the dose of didanosine delayed-release capsules should be adjusted to compensate for the slower rate of elimination. The recommended doses and dosing intervals of didanosine delayed-release capsules in adult patients with renal insufficiency are presented in Table 2.

Table 2: Recommended Dosage in Patients with Renal Impairment by Body Weight
Creatinine Clearance; (mL/min) | Dosage (mg)
 | at least 60 kg | less than 60 kg
at least 60 | 400 once daily | 250 once daily
30 to 59 | 200 once daily | 125 once daily
10 to 29 | 125 once daily | 125 once daily
less than 10 | 125 once daily

Pediatric Patients

Urinary excretion is also a major route of elimination of didanosine in pediatric patients, therefore the clearance of didanosine may be altered in pediatric patients with renal impairment. Although there are insufficient data to recommend a specific dose adjustment of didanosine delayed-release capsules in this patient population, a reduction in the dose should be considered (see Table 2).

Patients Requiring Continuous Ambulatory Peritoneal Dialysis (CAPD) or Hemodialysis

For patients requiring CAPD or hemodialysis, follow dosing recommendations for patients with creatinine clearance of less than 10 mL/min, shown in Table 2. It is not necessary to administer a supplemental dose of didanosine following hemodialysis.

2.3 Dose Adjustment

Concomitant Therapy with Tenofovir Disoproxil Fumarate

In patients who are also taking tenofovir disoproxil fumarate, a dose reduction of didanosine delayed-release capsules to 250 mg (adults weighing at least 60 kg with creatinine clearance of at least 60 mL/min) or 200 mg (adults weighing less than 60 kg with creatinine clearance of at least 60 mL/min) once daily taken together with tenofovir disoproxil fumarate and a light meal (400 kcalories or less, 20% fat or less) or in the fasted state is recommended. The appropriate dose of didanosine delayed-release capsules coadministered with tenofovir disoproxil fumarate in patients with creatinine clearance of less than 60 mL/min has not been established [see Drug Interactions (7) and Clinical Pharmacology (12.3)].

Hepatic Impairment

No dose adjustment is required in patients with hepatic impairment [see Warnings and Precautions (5.3) and Clinical Pharmacology (12.3)].

3 DOSAGE FORMS AND STRENGTHS

Didanosine Delayed-Release Capsules are available as:

200 mg: Two-piece hard gelatin capsule with green opaque cap and white opaque body filled with white pellets. Imprinted in black ink barr over 200 mg on one piece and 588 on the other piece.

250 mg: Two-piece hard gelatin capsule with blue opaque cap and white opaque body filled with white pellets. Imprinted in black ink barr over 250 mg on one piece and 589 on the other piece.

400 mg: Two-piece hard gelatin capsule with red opaque cap and white opaque body filled with white pellets. Imprinted in black ink barr over 400 mg on one piece and 590 on the other piece.

4 CONTRAINDICATIONS

These recommendations are based on either drug interaction studies or observed clinical toxicities.

4.1 Allopurinol

Coadministration of didanosine and allopurinol is contraindicated because systemic exposures of didanosine are increased, which may increase didanosine-associated toxicity [see Clinical Pharmacology (12.3)].

4.2 Ribavirin

Coadministration of didanosine and ribavirin is contraindicated because exposures of the active metabolite of didanosine (dideoxyadenosine 5’-triphosphate) are increased. Fatal hepatic failure, as well as peripheral neuropathy, pancreatitis, and symptomatic hyperlactatemia/lactic acidosis have been reported in patients receiving both didanosine and ribavirin.

5 WARNINGS AND PRECAUTIONS

5.1 Pancreatitis

Fatal and nonfatal pancreatitis has occurred during therapy with didanosine used alone or in combination regimens in both treatment-naive and treatment-experienced patients, regardless of degree of immunosuppression. Didanosine delayed-release capsules should be suspended in patients with signs or symptoms of pancreatitis and discontinued in patients with confirmed pancreatitis. Patients treated with didanosine delayed-release capsules in combination with stavudine may be at increased risk for pancreatitis.

When treatment with life-sustaining drugs known to cause pancreatic toxicity is required, suspension of didanosine delayed-release capsules therapy is recommended. In patients with risk factors for pancreatitis, didanosine delayed-release capsules should be used with extreme caution and only if clearly indicated. Patients with advanced HIV-1 infection, especially the elderly, are at increased risk of pancreatitis and should be followed closely. Patients with renal impairment may be at greater risk for pancreatitis if treated without dose adjustment. The frequency of pancreatitis is dose related [see Adverse Reactions (6)].

5.2 Lactic Acidosis/Severe Hepatomegaly with Steatosis

Lactic acidosis and severe hepatomegaly with steatosis, including fatal cases, have been reported with the use of nucleoside analogues alone or in combination, including didanosine and other antiretrovirals. A majority of these cases have been in women. Obesity and prolonged nucleoside exposure may be risk factors. Fatal lactic acidosis has been reported in pregnant women who received the combination of didanosine and stavudine with other antiretroviral agents. The combination of didanosine and stavudine should be used with caution during pregnancy and is recommended only if the potential benefit clearly outweighs the potential risk [see Use in Specific Populations (8.1)]. Particular caution should be exercised when administering didanosine delayed-release capsules to any patient with known risk factors for liver disease; however, cases have also been reported in patients with no known risk factors. Treatment with didanosine delayed-release capsules should be suspended in any patient who develops clinical signs or symptoms with or without laboratory findings consistent with symptomatic hyperlactatemia, lactic acidosis, or pronounced hepatotoxicity (which may include hepatomegaly and steatosis even in the absence of marked transaminase elevations).

5.3 Hepatic Toxicity

The safety and efficacy of didanosine delayed-release capsules have not been established in HIV-infected patients with significant underlying liver disease. During combination antiretroviral therapy, patients with preexisting liver dysfunction, including chronic active hepatitis, have an increased frequency of liver function abnormalities, including severe and potentially fatal hepatic adverse events, and should be monitored according to standard practice. If there is evidence of worsening liver disease in such patients, interruption or discontinuation of treatment must be considered.

Hepatotoxicity and hepatic failure resulting in death were reported during postmarketing surveillance in HIV-infected patients treated with hydroxyurea and other antiretroviral agents. Fatal hepatic events were reported most often in patients treated with the combination of hydroxyurea, didanosine, and stavudine. This combination should be avoided [see Adverse Reactions (6)].

5.4 Non-cirrhotic Portal Hypertension

Postmarketing cases of non-cirrhotic portal hypertension have been reported, including cases leading to liver transplantation or death. Cases of didanosine-associated non-cirrhotic portal hypertension were confirmed by liver biopsy in patients with no evidence of viral hepatitis. Onset of signs and symptoms ranged from months to years after start of didanosine therapy. Common presenting features included elevated liver enzymes, esophageal varices, hematemesis, ascites, and splenomegaly.

Patients receiving didanosine delayed-release capsules should be monitored for early signs of portal hypertension (eg, thrombocytopenia and splenomegaly) during routine medical visits. Appropriate laboratory testing including liver enzymes, serum bilirubin, albumin, complete blood count, and international normalized ratio (INR) and ultrasonography should be considered. Didanosine delayed-release capsules should be discontinued in patients with evidence of non-cirrhotic portal hypertension.

5.5 Peripheral Neuropathy

Peripheral neuropathy, manifested by numbness, tingling, or pain in the hands or feet, has been reported in patients receiving didanosine therapy. Peripheral neuropathy has occurred more frequently in patients with advanced HIV disease, in patients with a history of neuropathy, or in patients being treated with neurotoxic drug therapy, including stavudine. Discontinuation of didanosine delayed-release capsules should be considered in patients who develop peripheral neuropathy [see Adverse Reactions (6)].

5.6 Retinal Changes and Optic Neuritis

Retinal changes and optic neuritis have been reported in patients taking didanosine. Periodic retinal examinations should be considered for patients receiving didanosine delayed-release capsules [see Adverse Reactions (6)].

5.7 Immune Reconstitution Syndrome

Immune reconstitution syndrome has been reported in patients treated with combination antiretroviral therapy, including didanosine delayed-release capsules. During the initial phase of combination antiretroviral treatment, patients whose immune system responds may develop an inflammatory response to indolent or residual opportunistic infections (such as Mycobacterium avium infection, cytomegalovirus, Pneumocystis jiroveci pneumonia [PCP], or tuberculosis), which may necessitate further evaluation and treatment.

Autoimmune disorders (such as Graves’ disease, polymyositis, and Guillain-Barré syndrome) have also been reported to occur in the setting of immune reconstitution; however, the time to onset is more variable, and can occur many months after initiation of treatment.

5.8 Fat Redistribution

Redistribution/accumulation of body fat including central obesity, dorsocervical fat enlargement (buffalo hump), peripheral wasting, facial wasting, breast enlargement, and “cushingoid appearance” have been observed in patients receiving antiretroviral therapy. The mechanism and long-term consequences of these events are currently unknown. A causal relationship has not been established.

6 ADVERSE REACTIONS

The following adverse reactions are discussed in greater detail in other sections:

- Pancreatitis [see Boxed Warning, Warnings and Precautions (5.1)]
- Lactic acidosis/severe hepatomegaly with steatosis [see Boxed Warning, Warnings and Precautions (5.2)]
- Hepatic toxicity [see Warnings and Precautions (5.3)]
- Non-cirrhotic portal hypertension [see Warnings and Precautions (5.4)]
- Peripheral neuropathy [see Warnings and Precautions (5.5)]
- Retinal changes and optic neuritis [see Warnings and Precautions (5.6)]

6.1 Clinical Trials Experience

Because clinical trials are conducted under widely varying conditions, adverse reaction rates observed in the clinical trials of a drug cannot be directly compared to rates in the clinical trials of another drug and may not reflect the rates observed in practice.

Adults

Study AI454-152 was a 48-week, randomized, open-label study comparing didanosine delayed-release capsules (400 mg once daily) plus stavudine (40 mg twice daily) plus nelfinavir (750 mg three times daily) to zidovudine (300 mg) plus lamivudine (150 mg) combination tablets twice daily plus nelfinavir (750 mg three times daily) in 511 treatment-naive patients. Selected clinical adverse reactions that occurred in combination with other antiretroviral agents are provided in Table 3.

Table 3: Selected Clinical Adverse Reactions, Study AI454-152
 | Percent of Patients,
Adverse Reactions | didanosine delayed-release capsules + stavudine + nelfinavir n = 258 | zidovudine/ lamivudine+ nelfinavir n = 253
Diarrhea | 57 | 58
Peripheral Neurologic Symptoms/Neuropathy | 25 | 11
Nausea | 24 | 36
Headache | 22 | 17
Rash | 14 | 12
Vomiting | 14 | 19
Pancreatitis (see below) | less than 1

In clinical trials using a buffered formulation of didanosine, pancreatitis resulting in death was observed in one patient who received didanosine plus stavudine plus nelfinavir, one patient who received didanosine plus stavudine plus indinavir, and 2 of 68 patients who received didanosine delayed-release capsules plus stavudine plus indinavir plus hydroxyurea. In an early access program, pancreatitis resulting in death was observed in one patient who received didanosine plus stavudine plus hydroxyurea plus ritonavir plus indinavir plus efavirenz [see Warnings and Precautions (5)].

The frequency of pancreatitis is dose related. In phase 3 studies with buffered formulations of didanosine, incidence ranged from 1% to 10% with doses higher than are currently recommended and 1% to 7% with recommended dose.

Selected laboratory abnormalities that occurred in a study of didanosine delayed-release capsules in combination with other antiretroviral agents are shown in Table 4.

Table 4: Selected Laboratory Abnormalities, Study AI454-152
 |  | Percent of Patients
 | didanosine delayed-release capsules + stavudine + nelfinavir n = 258 |  | zidovudine/lamivudine + nelfinavir n = 253
Parameter | Grades 3 to 4 [Greater than 5 x ULN for SGOT and SGPT, at least 2.1 x ULN for lipase, and at least 2.6 x ULN for bilirubin (ULN = upper limit of normal).] | All Grades | Grades 3 to 4 | All Grades
SGOT (AST) | 5 | 46 | 5 | 19
SGPT (ALT) | 6 | 44 | 5 | 22
Lipase | 5 | 23 | 2 | 13
Bilirubin | less than 1 | 9 | less than 1 | 3

Pediatric Patients

In clinical trials, 743 pediatric patients between 2 weeks and 18 years of age have been treated with didanosine. Adverse reactions and laboratory abnormalities reported to occur in these patients were generally consistent with the safety profile of didanosine in adults.

In pediatric phase 1 studies, pancreatitis occurred in 2 of 60 (3%) patients treated at entry doses below 300 mg/m^2/day and in 5 of 38 (13%) patients treated at higher doses. In study ACTG 152, pancreatitis occurred in none of the 281 pediatric patients who received didanosine 120 mg/m^2 every 12 hours and in less than 1% of the 274 pediatric patients who received didanosine 90 mg/m^2 every 12 hours in combination with zidovudine [see Clinical Studies (14)].

Retinal changes and optic neuritis have been reported in pediatric patients.

6.2 Postmarketing Experience

The following adverse reactions have been identified during postapproval use of didanosine. Because they are reported voluntarily from a population of unknown size, estimates of frequency cannot be made. These reactions have been chosen for inclusion due to their seriousness, frequency of reporting, causal connection to didanosine, or a combination of these factors.

Blood and Lymphatic System Disorders - anemia, leukopenia, and thrombocytopenia.

Body as a Whole - abdominal pain, alopecia, anaphylactoid reaction, asthenia, chills/fever, pain, and redistribution/accumulation of body fat [see Warnings and Precautions (5.8) ].

Digestive Disorders - anorexia, dyspepsia, and flatulence.

Exocrine Gland Disorders - pancreatitis (including fatal cases) [see Warnings and Precautions
(5.1)], sialoadenitis, parotid gland enlargement, dry mouth, and dry eyes.

Hepatobiliary Disorders - symptomatic hyperlactatemia/lactic acidosis and hepatic steatosis [see Warnings and Precautions (5.2)]; non-cirrhotic portal hypertension [see Warnings and Precautions (5.4)]; hepatitis and liver failure.

Metabolic Disorders - diabetes mellitus, elevated serum alkaline phosphatase level, elevated serum amylase level, elevated serum gamma-glutamyltransferase level, elevated serum uric acid level, hypoglycemia, and hyperglycemia.

Musculoskeletal Disorders - myalgia (with or without increases in creatine kinase), rhabdomyolysis including acute renal failure and hemodialysis, arthralgia, and myopathy.

Ophthalmologic Disorders - retinal depigmentation and optic neuritis [see Warnings and Precautions (5.6)].

Use with Stavudine- and Hydroxyurea-Based Regimens

When didanosine is used in combination with other agents with similar toxicities, the incidence of these toxicities may be higher than when didanosine is used alone. Thus, patients treated with didanosine delayed-release capsules in combination with stavudine, with or without hydroxyurea, may be at increased risk for pancreatitis and hepatotoxicity, which may be fatal, and severe peripheral neuropathy [see Warnings and Precautions (5)]. The combination of didanosine delayed-release capsules and hydroxyurea, with or without stavudine, should be avoided.

7 DRUG INTERACTIONS

7.1 Established Drug Interactions

Clinical recommendations based on the results of drug interaction studies are listed in Table 5. Pharmacokinetic results of drug interaction studies are shown in Tables 9 to 12 [see Contraindications (4.1 and 4.2), Clinical Pharmacology (12.3)].

Table 5: Established Drug Interactions Based on Studies with Didanosine Delayed-Release Capsules or Studies with Buffered Formulations of Didanosine and Expected to Occur with Didanosine Delayed-Release Capsules
Drug | Effect | Clinical Comment
ganciclovir | ↑didanosine concentration | If there is no suitable alternative to ganciclovir, then use in combination with didanosine delayed-release capsules with caution. Monitor for didanosine-associated toxicity.
methadone | ↓didanosine concentration | If coadministration of methadone and didanosine is necessary, the recommended formulation of didanosine is didanosine delayed-release capsules. Patients should be closely monitored for adequate clinical response when didanosine delayed-release capsules are coadministered with methadone, including monitoring for changes in HIV RNA viral load. Do not coadminister methadone with didanosine pediatric powder due to significant decreases in didanosine concentrations.
nelfinavir | No interaction 1 hour after didanosine | Administer nelfinavir 1 hour after didanosine delayed-release capsules.
tenofovir disoproxil; fumarate | ↑didanosine concentration | A dose reduction of didanosine delayed-release capsules to the following dosage once daily taken together with tenofovir disoproxil fumarate and a light meal (400 kcalories or less and 20% fat or less) or in the fasted state is recommended.; - 250 mg (adults weighing at least 60 kg with creatinine clearance of at least 60 mL/min) - 200 mg (adults weighing less than 60 kg with creatinine clearance of at least 60 mL/min); Patients should be monitored for didanosine-associated toxicities and clinical response.
↑ Indicates increase.
↓ Indicates decrease.

Exposure to didanosine is increased when coadministered with tenofovir disoproxil fumarate
[Table 5 and see Clinical Pharmacokinetics (12.3, Tables 9 and 10)]. Increased exposure may cause or worsen didanosine-related clinical toxicities, including pancreatitis, symptomatic hyperlactatemia/lactic acidosis, and peripheral neuropathy. Coadministration of tenofovir disoproxil fumarate with didanosine delayed-release capsules should be undertaken with caution, and patients should be monitored closely for didanosine-related toxicities and clinical response. Didanosine delayed-release capsules should be suspended if signs or symptoms of pancreatitis, symptomatic hyperlactatemia, or lactic acidosis develop [see Dosage and Administration (2.3), Warnings and Precautions (5)]. Suppression of CD4 cell counts has been observed in patients receiving tenofovir disoproxil fumarate with didanosine at a dose of 400 mg daily.

7.2 Predicted Drug Interactions

Predicted drug interactions with didanosine delayed-release capsules are listed in Table 6.

Table 6: Predicted Drug Interactions with Didanosine Delayed-Release Capsules
Drug or Drug Class | Effect | Clinical Comment
Drugs that may cause pancreatic toxicity | ↑risk of pancreatitis | Use only with extreme caution.
Neurotoxic drugs | ↑risk of neuropathy | Use with caution.
↑ Indicates increase.

8 USE IN SPECIFIC POPULATIONS

8.1 Pregnancy

Pregnancy Category B

Reproduction studies have been performed in rats and rabbits at doses up to 12 and 14.2 times the estimated human exposure (based upon plasma levels), respectively, and have revealed no evidence of impaired fertility or harm to the fetus due to didanosine. At approximately 12 times the estimated human exposure, didanosine was slightly toxic to female rats and their pups during mid and late lactation. These rats showed reduced food intake and body weight gains but the physical and functional development of the offspring was not impaired and there were no major changes in the F2 generation. A study in rats showed that didanosine and/or its metabolites are transferred to the fetus through the placenta. Animal reproduction studies are not always predictive of human response.

There are no adequate and well-controlled studies of didanosine in pregnant women. Didanosine should be used during pregnancy only if the potential benefit justifies the potential risk.

Fatal lactic acidosis has been reported in pregnant women who received the combination of didanosine and stavudine with other antiretroviral agents. It is unclear if pregnancy augments the risk of lactic acidosis/hepatic steatosis syndrome reported in nonpregnant individuals receiving nucleoside analogues [see Warnings and Precautions (5.2)]. The combination of didanosine and stavudine should be used with caution during pregnancy and is recommended only if the potential benefit clearly outweighs the potential risk. Healthcare providers caring for HIV-infected pregnant women receiving didanosine should be alert for early diagnosis of lactic acidosis/hepatic steatosis syndrome.

Antiretroviral Pregnancy Registry

To monitor maternal-fetal outcomes of pregnant women exposed to didanosine and other antiretroviral agents, an Antiretroviral Pregnancy Registry has been established. Physicians are encouraged to register patients by calling 1-800-258-4263.

8.3 Nursing Mothers

The Centers for Disease Control and Prevention recommend that HIV-infected mothers not breast-feed their infants to avoid risking postnatal transmission of HIV. A study in rats showed that following oral administration, didanosine and/or its metabolites were excreted into the milk of lactating rats. It is not known if didanosine is excreted in human milk. Because of both the potential for HIV transmission and the potential for serious adverse reactions in nursing infants, mothers should be instructed not to breast-feed if they are receiving didanosine.

8.4 Pediatric Use

Use of didanosine in pediatric patients from 2 weeks of age through adolescence is supported by evidence from adequate and well-controlled studies of didanosine in adult and pediatric patients [see Dosage and Administration (2), Adverse Reactions (6.1), Clinical Pharmacology (12.3), and Clinical Studies (14)]. Additional pharmacokinetic studies in pediatric patients support use of didanosine delayed-release capsules in pediatric patients who weigh at least 20 kg.

8.5 Geriatric Use

In an Expanded Access Program using a buffered formulation of didanosine for the treatment of advanced HIV infection, patients aged 65 years and older had a higher frequency of pancreatitis (10%) than younger patients (5%) [see Warnings and Precautions (5.1)]. Clinical studies of didanosine, including those for didanosine delayed-release capsules, did not include sufficient numbers of subjects aged 65 years and over to determine whether they respond differently than younger subjects. Didanosine is known to be substantially excreted by the kidney, and the risk of toxic reactions to this drug may be greater in patients with impaired renal function. Because elderly patients are more likely to have decreased renal function, care should be taken in dose selection. In addition, renal function should be monitored and dosage adjustments should be made accordingly [see Dosage and Administration (2.2)].

8.6 Renal Impairment

Patients with renal impairment (creatinine clearance of less than 60 mL/min) may be at greater risk of toxicity from didanosine due to decreased drug clearance [see Clinical Pharmacology (12.3)]. A dose reduction is recommended for these patients [see Dosage and Administration (2)].

10 OVERDOSAGE

There is no known antidote for didanosine overdosage. In phase 1 studies, in which buffered formulations of didanosine were initially administered at doses ten times the currently recommended dose, toxicities included: pancreatitis, peripheral neuropathy, diarrhea, hyperuricemia, and hepatic dysfunction. Didanosine is not dialyzable by peritoneal dialysis, although there is some clearance by hemodialysis [see Clinical Pharmacology (12.3)].

11 DESCRIPTION

Didanosine delayed-release capsules are an enteric-coated formulation of didanosine, USP, a synthetic purine nucleoside analogue active against HIV-1. Each didanosine delayed-release capsule containing enteric-coated pellets, for oral administration, contains 200 mg, 250 mg or 400 mg of didanosine, USP. In addition each capsule contains the following inactive ingredients: black iron oxide, croscarmellose sodium, D&C yellow no. 10 aluminum lake, FD&C blue no. 1, FD&C blue no. 1 aluminum lake, FD&C blue no. 2 aluminum lake, FD&C red no. 40 aluminum lake, gelatin, hydroxypropyl cellulose, hypromellose, methacrylic acid copolymer dispersion, microcrystalline cellulose, polydextrose, polyethylene glycol, propylene glycol, shellac glaze, silicon dioxide, sodium hydroxide, talc, titanium dioxide, triacetin and triethyl citrate. The 200 mg and 400 mg capsule also contains D&C red no. 33 and FD&C yellow no. 6, and the 250 mg also contains D&C red no. 28.

The chemical name for didanosine is 2' ,3' -dideoxyinosine. The structural formula is:

C10H12N4O3 M.W. 236.2

Didanosine is a white crystalline powder. The aqueous solubility of didanosine at 25° C and pH of approximately 6 is 27.3 mg/mL. Didanosine is unstable in acidic solutions. For example, at pH less than 3 and 37° C, 10% of didanosine decomposes to hypoxanthine in less than 2 minutes. In didanosine delayed-release capsules, an enteric coating is used to protect didanosine from degradation by stomach acid.

12 CLINICAL PHARMACOLOGY

12.1 Mechanism of Action

Didanosine is an antiviral agent [see Clinical Pharmacology (12.4)].

12.3 Pharmacokinetics

The pharmacokinetic parameters of didanosine in HIV-infected adult and pediatric patients are summarized in Table 7, by weight ranges that correspond to recommended doses (Table 1). Didanosine is rapidly absorbed, with peak plasma concentrations generally observed from 0.25 to 1.50 hours following oral dosing with a buffered formulation. Increases in plasma didanosine concentrations were dose proportional over the range of 50 to 400 mg. In adults, the mean (± standard deviation) oral bioavailability following single oral dosing with a buffered formulation is 42 (±12)%. After oral administration, the urinary recovery of didanosine is approximately 18 (±8)% of the dose. The CSF-plasma ratio following IV administration is 21 (±0.03)%. Steady-state pharmacokinetic parameters did not differ significantly from values obtained after a single dose. Binding of didanosine to plasma proteins in vitro was low (less than 5%). Based on data from in vitro and animal studies, it is presumed that the metabolism of didanosine in man occurs by the same pathways responsible for the elimination of endogenous purines.

Table 7: Pharmacokinetic Parameters for Didanosine in HIV-infected Patients
 | Pediatrics |  | Adults
Parameter | 20 kg to less than 25 kg n = 10 | 25 kg to less than 60 kg n = 17 | At least 60 kg n = 7 | At least 60 kg n = 44
Apparent clearance (L/h) | 89.5 + 21.6 | 116.2 + 38.6 | 196 + 55.8 | 174.5 + 69.7
Apparent volume of distribution (L) | 98.1 + 30.2 | 154.7 + 55 | 363 + 137.7 | 308.3 + 164.3
Elimination half-life (h) | 0.75 + 0.13 | 0.92 + 0.09 | 1.26 + 0.19 | 1.19 + 0.21
Steady-state (AUC) (mg•h/L) | 2.38 + 0.66 | 2.36 + 0.70 | 2.25 + 0.89 | 2.65 + 1.07

Comparison of Didanosine Formulations

In didanosine delayed-release capsules, the active ingredient, didanosine, is protected against degradation by stomach acid by the use of an enteric coating on the pellets in the capsule. The enteric coating dissolves when the pellets empty into the small intestine, the site of drug absorption. With buffered formulations of didanosine, administration with antacid provides protection from degradation by stomach acid.

In healthy volunteers, as well as subjects infected with HIV-1, the AUC is equivalent for didanosine administered as the didanosine delayed-release capsules formulation relative to a buffered tablet formulation. The peak plasma concentration (Cmax) of didanosine, administered as didanosine delayed-release capsules, is reduced approximately 40% relative to didanosine buffered tablets. The time to the peak concentration (Tmax) increases from approximately 0.67 hours for didanosine buffered tablets to 2 hours for didanosine delayed-release capsules.

Effect of Food

In the presence of food, the Cmax and AUC for didanosine delayed-release capsules were reduced by approximately 46% and 19%, respectively, compared to the fasting state [see Dosage and Administration (2)]. Didanosine delayed-release capsules should be taken on an empty stomach.

Special Populations

Renal Insufficiency: Data from two studies using a buffered formulation of didanosine indicated that the apparent oral clearance of didanosine decreased and the terminal elimination half-life increased as creatinine clearance decreased (see Table 8). Following oral administration, didanosine was not detectable in peritoneal dialysate fluid (n = 6); recovery in hemodialysate (n = 5) ranged from 0.6% to 7.4% of the dose over a 3 to 4 hour dialysis period. The absolute bioavailability of didanosine was not affected in patients requiring dialysis. [See Dosage and Administration (2.2).]

Table 8: Mean ± SD Pharmacokinetic Parameters for Didanosine Following a Single Oral Dose of a Buffered Formulation
 | Creatinine Clearance (mL/min)
Parameter | at least 90 n = 12 | 60-90 n = 6 | 30-59 n = 6 | 10-29 n = 3 | Dialysis Patients n = 11
CLcr (mL/min) | 112 + 22 | 68 + 8 | 46 + 8 | 13 + 5 | ND
CL/F (mL/min) | 2164 + 638 | 1566 + 833 | 1023 + 378 | 628 + 104 | 543 + 174
CLR (mL/min) | 458 + 164 | 247 + 153 | 100 + 44 | 20 + 8 | less than 10
T1/2 (h) | 1.42 + 0.33 | 1.59 + 0.13 | 1.75 + 0.43 | 2 + 0.3 | 4.1 + 1.2
ND = not determined due to anuria.
CLcr = creatinine clearance.
CL/F = apparent oral clearance.
CLR = renal clearance.

Hepatic Impairment: The pharmacokinetics of didanosine have been studied in 12 non-HIV-infected subjects with moderate (n = 8) to severe (n = 4) hepatic impairment (Child-Pugh Class B or C). Mean AUC and Cmax values following a single 400 mg dose of didanosine were approximately 13% and 19% higher, respectively, in patients with hepatic impairment compared to matched healthy subjects. No dose adjustment is needed, because a similar range and distribution of AUC and Cmax values was observed for subjects with hepatic impairment and matched healthy controls. [See Dosage and Administration (2.3)].

Pediatric Patients: The pharmacokinetics of didanosine have been evaluated in HIV-exposed and HIV-infected pediatric patients from birth to adulthood.

A population pharmacokinetic analysis was conducted on pooled didanosine plasma concentration data from 9 clinical trials in 106 pediatric (neonate to 18 years of age) and 45 adult patients (greater than 18 years of age). Results showed that body weight is the primary factor associated with oral clearance. Based on the data analyzed, dosing schedule (once versus twice daily) and formulation (powder for oral solution, tablet, and delayed-release capsule) did not have an effect on oral clearance. Didanosine exposure similar to that at recommended adult doses can be achieved in pediatric patients with a weight-based dosing scheme [see Dosage and Administration (2)].

Geriatric Patients: Didanosine pharmacokinetics have not been studied in patients over 65 years of age [see Use in Specific Populations (8.5)].

Gender: The effects of gender on didanosine pharmacokinetics have not been studied.

Drug Interactions

Tables 9 and 10 summarize the effects on AUC and Cmax, with a 90% confidence interval (CI) when available, following coadministration of didanosine delayed-release capsules with a variety of drugs. For clinical recommendations based on drug interaction studies for drugs in bold font [see Dosage and Administration (2.3) and Drug Interactions (7.1)].

Table 9: Results of Drug Interaction Studies with Didanosine: Effects of Coadministered Drug on Didanosine Plasma AUC and Cmax Values
 |  |  | % Change of Didanosine; Pharmacokinetic Parameters
Drug Didanosine Dosage n |  |  | AUC of Didanosine; (90% CI) | Cmax of Didanosine; (90% CI)
tenofovir, [All studies conducted in healthy volunteers at least 60 kg with creatinine clearance of at least 60 mL/min.] , [Tenofovir disoproxil fumarate.] 300 mg; once daily with a light meal [373 kcalories, 8.2 grams fat.]; tenofovir, , 300 mg; once daily with a light meal; tenofovir, , 300 mg; once daily with a light meal; methadone, chronic; maintenance dose | 400 mg single dose; fasting 2 hours before tenofovir; 400 mg single dose; with tenofovir and a light meal; 200 mg single dose; with tenofovir and a light meal; 250 mg single dose; with tenofovir and a light meal; 325 mg single dose; with tenofovir and a light meal; 400 mg single dose | 26; 25; 33; 33; 33; 15, 16 | ↑ 48%; (31, 67%); ↑ 60%; (44, 79%); ↑ 16%; (6, 27%) [Compared with didanosine delayed-release capsules 250 mg administered alone under fasting conditions.]; ↔; (-13, 5%) [Compared with didanosine delayed-release capsules 400 mg administered alone under fasting conditions.]; ↑ 13%; (3, 24%); ↓ 17%; (-29, -2%) | ↑ 48%; (25, 76%); ↑ 64%; (41, 89%); ↓ 12%; (-25, 3%); ↓ 20%; (-32, -7%); ↓ 11%; (-24, 4%); ↓ 16%; (-33, 4%)
↑ Indicates increase.
↓ Indicates decrease.
↔ Indicates no change, or mean increase or decrease of less than 10%.

Table 10: Results of Drug Interaction Studies with Didanosine Delayed-Release Capsule: Effects of Didanosine on Coadministered Drug Plasma AUC and Cmax Values
 |  |  | % Change of Coadministered Drug Pharmacokinetic Parameters,
Drug Didanosine Dosage n |  |  | AUC of Coadministered Drug; (90% CI) | Cmax of Coadministered Drug; (90% CI)
ciprofloxacin, 750 mg; single dose; indinavir, 800 mg; single dose; ketoconazole, 200 mg; single dose; tenofovir, [Tenofovir disoproxil fumarate.] 300 mg; once daily with a light meal [373 kcalories, 8.2 grams fat.]; tenofovir, 300 mg; once daily with a light meal | 400 mg single dose; 400 mg single dose; 400 mg single dose; 400 mg single dose; fasting 2 hours before; tenofovir; 400 mg single dose; with tenofovir and; a light meal | 16; 23; 21; 25; 25 | ↔; ↔; ↔; ↔; ↔ | ↔; ↔; ↔; ↔; ↔
↔ Indicates no change, or mean increase or decrease of less than 10%.

Didanosine Buffered Formulations: Tables 11 and 12 summarize the effects on AUC and Cmax, with a 90% or 95% CI when available, following coadministration of buffered formulations of didanosine delayed-release capsules with a variety of drugs. The results of these studies may be expected to apply to didanosine. For most of the listed drugs, no clinically significant pharmacokinetic interactions were noted. For clinical recommendations based on drug interaction studies for drugs in bold font [see Dosage and Administration (2.3 for Concomitant Therapy with Tenofovir Disoproxil Fumarate), Contraindications (4.1) and Drug Interactions (7.1)].

Table 11: Results of Drug Interaction Studies with Buffered Formulations of Didanosine: Effects of Coadministered Drug of Didanosine Plasma AUC and Cmax Values
 |  |  | % Change of Didanosine; Pharmacokinetic Parameters
Drug Didanosine Dosage n |  |  | AUC of Didanosine; (95% CI) | Cmax of Didanosine; (95% CI)
allopurinol,; renally impaired, 300 mg/day; healthy volunteer, 300 mg/day for 7 days; ganciclovir, 1000 mg every 8 hours, 2 hours after didanosine; ciprofloxacin, 750 mg every 12 hours for 3 days, 2 hours before didanosine; indinavir, 800 mg single dose simultaneous; 1 hour before didanosine; ketoconazole, 200 mg/day for 4 days, 2 hours before didanosine; loperamide, 4 mg every 6 hours for 1 day; metoclopramide, 10 mg single dose; ranitidine, 150 mg single dose, 2 hours before didanosine; rifabutin, 300 mg or 600 mg/day for 12 days; ritonavir, 600 mg every 12 hours for 4 days; stavudine, 40 mg every 12 hours for 4 days; sulfamethoxazole, 1000 mg single dose; trimethoprim, 200 mg single dose; zidovudine, 200 mg every 8 hours for 3 days | 200 mg single dose; 400 mg single dose; 200 mg every; 12 hours; 200 mg every; 12 hours for 3 days; 200 mg single dose; 200 mg single dose; 375 mg every; 12 hours for 4 days; 300 mg single dose; 300 mg single dose; 375 mg single dose; 167 mg or 250 mg every 12 hours for 12 days; 200 mg every 12 hours for 4 days; 100 mg every 12 hours for 4 days; 200 mg single dose; 200 mg single dose; 200 mg every; 12 hours for 3 days | 2; 14; 12; 8 [HIV-infected patients.]; 16; 16; 12; 12; 12; 12; 11; 12; 10; 8; 8; 6 | ↑ 312%; ↑ 113%; ↑ 111%; ↓ 16%; ↔; ↓ 17%; (-27, -7%) [90% CI.]; ↔; ↔; ↔; ↑ 14%; ↑ 13%; (-1, 27%); ↓ 13%; (0, 23%); ↔; ↔; ↔; ↔ | ↑ 232%; ↑ 69%; NA; ↓ 28%; ↔; ↓ 13%; (-28, 5%); ↓ 12%; ↓ 23%; ↑ 13%; ↑ 13%; ↑ 17%; (-4, 38%); ↓ 16%; (5, 26%); ↔; ↔; ↑ 17%; (-23, 77%); ↔
↑ Indicates increase.
↓ Indicates decrease.
↔ Indicates no change, or mean increase or decrease of less than 10%.

NA = Not available.

Table 12: Results of Drug Interaction Studies with Buffered Formulations of Didanosine: Effects of Didanosine on Coadministered Drug Plasma AUC and Cmax Values
 |  |  | % Change of Coadministered Drug Pharmacokinetic Parameters
Drug Didanosine Dosage n |  |  | AUC of Coadministered Drug; (95% CI) | Cmax of Coadministered Drug; (95% CI)
dapsone, 100 mg single dose; ganciclovir, 1000 mg every 8 hours, 2 hours after didanosine; nelfinavir, 750 mg single dose, 1 hour after didanosine; ranitidine, 150 mg single dose, 2 hours before didanosine; ritonavir, 600 mg every 12 hours for 4 days; stavudine, 40 mg every 12 hours for 4 days; sulfamethoxazole, 1000 mg single dose; trimethoprim, 200 mg single dose; zidovudine, 200 mg every 8 hours for 3 days | 200 mg every 12 hours; for 14 days; 200 mg every 12 hours; 200 mg single dose; 375 mg single dose; 200 mg every 12 hours; for 4 days; 100 mg every 12 hours; for 4 days; 200 mg single dose; 200 mg single dose; 200 mg every 12 hours; for 3 days | 6 [HIV-infected patients.]; 12; 10; 12; 12; 10; 8; 8; 6 | ↔; ↓ 21%; ↑ 12%; ↓ 16%; ↔; ↔; ↓ 11%; (-17, -4%); ↑ 10%; (-9, 34%); ↓ 10%; (-27, 11%) | ↔; NA; ↔; ↔; ↔; ↑ 17%; ↓ 12%; (-28, 8%); ↓ 22%; (-59, 49%); ↓ 16.5%; (-53, 47%)
↑ Indicates increase.
↓ Indicates decrease.
↔ Indicates no change, or mean increase or decrease of less than 10%.
NA = Not available.

NA = Not available.

12.4 Microbiology

Mechanism of Action

Didanosine is a synthetic nucleoside analogue of the naturally occurring nucleoside deoxyadenosine in which the 3’-hydroxyl group is replaced by hydrogen. Intracellularly, didanosine is converted by cellular enzymes to the active metabolite, dideoxyadenosine 5’-triphosphate. Dideoxyadenosine 5’-triphosphate inhibits the activity of HIV-1 reverse transcriptase both by competing with the natural substrate, deoxyadenosine 5’-triphosphate, and by its incorporation into viral DNA causing termination of viral DNA chain elongation.

Antiviral Activity in Cell Culture

The anti-HIV-1 activity of didanosine was evaluated in a variety of HIV-1 infected lymphoblastic cell lines and monocyte/macrophage cell cultures. The concentration of drug necessary to inhibit viral replication by 50% (EC50) ranged from 2.5 to 10 μM
(1 μM = 0.24 mcg/mL) in lymphoblastic cell lines and 0.01 to 0.1 μM in monocyte/macrophage cell cultures.

Resistance

HIV-1 isolates with reduced sensitivity to didanosine have been selected in cell culture and were also obtained from patients treated with didanosine. Genetic analysis of isolates from didanosine-treated patients showed mutations in the reverse transcriptase gene that resulted in the amino acid substitutions K65R, L74V, and M184V. The L74V substitution was most frequently observed in clinical isolates. Phenotypic analysis of HIV-1 isolates from 60 patients (some with prior zidovudine treatment) receiving 6 to 24 months of didanosine monotherapy showed that isolates from 10 of 60 patients exhibited an average of a 10-fold decrease in susceptibility to didanosine in cell culture compared to baseline isolates. Clinical isolates that exhibited a decrease in didanosine susceptibility harbored one or more didanosine resistance-associated substitutions.

Cross-resistance

HIV-1 isolates from 2 of 39 patients receiving combination therapy for up to 2 years with didanosine and zidovudine exhibited decreased susceptibility to didanosine, lamivudine, stavudine, zalcitabine, and zidovudine in cell culture. These isolates harbored five substitutions (A62V, V75I, F77L, F116Y, and Q151M) in the reverse transcriptase gene. In data from clinical studies, the presence of thymidine analogue mutations (M41L, D67N, L210W, T215Y, K219Q) has been shown to decrease the response to didanosine.

13 NONCLINICAL TOXICOLOGY

13.1 Carcinogenesis, Mutagenesis, Impairment of Fertility

Lifetime carcinogenicity studies were conducted in mice and rats for 22 and 24 months, respectively. In the mouse study, initial doses of 120, 800, and 1200 mg/kg/day for each sex were lowered after 8 months to 120, 210, and 210 mg/kg/day for females and 120, 300, and 600 mg/kg/day for males. The two higher doses exceeded the maximally tolerated dose in females and the high dose exceeded the maximally tolerated dose in males. The low dose in females represented 0.68-fold maximum human exposure and the intermediate dose in males represented 1.7-fold maximum human exposure based on relative AUC comparisons. In the rat study, initial doses were 100, 250, and 1000 mg/kg/day, and the high dose was lowered to 500 mg/kg/day after 18 months. The upper dose in male and female rats represented 3-fold maximum human exposure.

Didanosine induced no significant increase in neoplastic lesions in mice or rats at maximally tolerated doses.

Didanosine was positive in the following genetic toxicology assays: 1) the Escherichia coli tester strain WP2 uvrA bacterial mutagenicity assay; 2) the L5178Y/TK+/- mouse lymphoma mammalian cell gene mutation assay; 3) the in vitro chromosomal aberrations assay in cultured human peripheral lymphocytes; 4) the in vitro chromosomal aberrations assay in Chinese Hamster Lung cells; and 5) the BALB/c 3T3 in vitro transformation assay. No evidence of mutagenicity was observed in an Ames Salmonella bacterial mutagenicity assay or in rat and mouse in vivo micronucleus assays.

13.2 Animal Toxicology and/or Pharmacology

Evidence of a dose-limiting skeletal muscle toxicity has been observed in mice and rats (but not in dogs) following long-term (greater than 90 days) dosing with didanosine at doses that were approximately 1.2 to 12 times the estimated human exposure. The relationship of this finding to the potential of didanosine to cause myopathy in humans is unclear. However, human myopathy has been associated with administration of didanosine and other nucleoside analogues.

14 CLINICAL STUDIES

14.1 Adult Patients

Study AI454-152 was a 48-week, randomized, open-label study comparing didanosine delayed-release capsules (400 mg once daily) plus stavudine (40 mg twice daily) plus nelfinavir (750 mg three times daily) to zidovudine (300 mg) plus lamivudine (150 mg) combination tablets twice daily plus nelfinavir (750 mg three times daily) in 511 treatment-naive patients, with a mean CD4 cell count of 411 cells/mm^3 (range 39 to 1105 cells/mm^3) and a mean plasma HIV-1 RNA of 4.71 log10 copies/mL (range 2.8 to 5.9 log10 copies/mL) at baseline. Patients were primarily males (72%) and Caucasian (53%) with a mean age of 35 years (range 18 to 73 years). The percentages of patients with HIV-1 RNA less than 400 and less than 50 copies/mL and outcomes of patients through 48 weeks are summarized in Figure 1 and Table 13, respectively.

Figure 1 Treatment Response Through Week 48*, AI454-152

○● didanosine + stavudine + nelfinavir, n = 258

∆▲ zidovudine/lamivudine + nelfinavir, n = 253

*Percent of patients at each time point who have HIV RNA < 400 or < 50 copies/mL and do not meet any criteria for treatment failure (e.g., virologic failure or discontinuation for any reason).

Table 13: Outcomes of Randomized Treatment Through Week 48, AI454-152
Outcome | Percent of Patients with HIV-1 RNA less than 400 copies/mL (less than 50 copies/mL)
Outcome | didanosine + stavudine + nelfinavir; n = 258 | zidovudine/lamivudine + nelfinavir; n = 253
Responder,; Virologic failure; Death or discontinued due to; disease progression; Discontinued due to adverse event; Discontinued due to other reasons | 55% (33%); 22% (45%); 1% (1%); 6% (6%); 16% (16%) | 56% (33%); 21% (43%); 2% (2%); 7% (7%); 15% (16%)

14.2 Pediatric Patients

Efficacy in pediatric patients was demonstrated in a randomized, double-blind, controlled study (ACTG 152, conducted 1991-1995) involving 831 patients 3 months to 18 years of age treated for more than 1.5 years with zidovudine (180 mg/m^2 every 6 hours), didanosine (120 mg/m^2 every 12 hours), or zidovudine (120 mg/m^2 every 6 hours) plus didanosine (90 mg/m^2 every 12 hours). Patients treated with didanosine or didanosine plus zidovudine had lower rates of HIV-1 disease progression or death compared with those treated with zidovudine alone.

16 HOW SUPPLIED/STORAGE AND HANDLING

Didanosine Delayed-Release Capsules are available as:

250 mg: Two-piece hard gelatin capsule with blue opaque cap and white opaque body filled with white pellets. Imprinted in black ink barr over 250 mg on one piece and 589 on the other piece. Available in bottles of 30 capsules NDC 54868-5464-0.

Storage

Store at 20° to 25°C (68° to 77°F) [See USP Controlled Room Temperature].

Keep container tightly closed.

KEEP THIS AND ALL MEDICATIONS OUT OF THE REACH OF CHILDREN.

17 PATIENT COUNSELING INFORMATION

See Medication Guide

17.1 Pancreatitis

Patients should be informed that a serious toxicity of didanosine, used alone and in combination regimens, is pancreatitis, which may be fatal.

17.2 Peripheral Neuropathy

Patients should be informed that peripheral neuropathy, manifested by numbness, tingling, or pain in hands or feet, may develop during therapy with didanosine delayed-release capsules. Patients should be counseled that peripheral neuropathy occurs with greatest frequency in patients with advanced HIV-1 disease or a history of peripheral neuropathy, and discontinuation of didanosine delayed-release capsules may be required if toxicity develops.

17.3 Lactic Acidosis and Severe Hepatomegaly with Steatosis

Patients should be informed that lactic acidosis and severe hepatomegaly with steatosis, including fatal cases, have been reported with the use of nucleoside analogues alone or in combination, including didanosine and other antiretrovirals.

17.4 Hepatic Toxicity

Patients should be informed that hepatotoxicity including fatal hepatic adverse events were reported in patients with preexisting liver dysfunction. The safety and efficacy of didanosine delayed-release capsules has not been established in HIV-infected patients with significant underlying liver disease.

17.5 Non-cirrhotic Portal Hypertension

Patients should be informed that non-cirrhotic portal hypertension has been reported in patients taking didanosine delayed-release capsules, including cases leading to liver transplantation or death.

17.6 Retinal Changes and Optic Neuritis

Patients should be informed that retinal changes and optic neuritis have been reported in adult and pediatric patients.

17.7 Fat Redistribution

Patients should be informed that redistribution or accumulation of body fat may occur in patients receiving antiretroviral therapy and that the cause and long-term health effects of these conditions are not known at this time.

17.8 Concomitant Therapy

Patients should be informed that when didanosine is used in combination with other agents with similar toxicities, the incidence of adverse events may be higher than when didanosine is used alone. These patients should be followed closely.

Patients should be cautioned about the use of medications or other substances, including alcohol, which may exacerbate didanosine delayed-release capsules toxicities.

17.9 General Information

Didanosine is not a cure for HIV-1 infection, and patients may continue to experience illnesses associated with HIV-1 infection, including opportunistic infections. Therefore, patients should remain under the care of a physician when using didanosine.

Patients should be advised to avoid doing things that can spread HIV-1 infection to others.

- Do not share needles or other injection equipment.
- Do not share personal items that can have blood or body fluids on them, like toothbrushes and razor blades.
- Do not have any kind of sex without protection. Always practice safe sex by using a latex or polyurethane condom or other barrier method to lower the chance of sexual contact with semen, vaginal secretions, or blood.
- Do not breast-feed. It is not known if didanosine can be passed to your baby in your breast milk and whether it could harm your baby. Also, mothers with HIV-1 should not breast-feed because HIV-1 can be passed to the baby in breast milk.

Patients should be instructed to swallow the capsule as a whole and to not open the capsule.

Patients should be instructed to not miss a dose but if they do, patients should take didanosine as soon as possible. Patients should be told that if it is almost time for the next dose, they should skip the missed dose and continue with the regular dosing schedule.

Patients should be instructed to contact a poison control center or emergency room right away in case of an overdose.

TEVA PHARMACEUTICALS USA
Sellersville, PA 18960
Rev. D 12/2011

Additional barcode labeling by:
Physicians Total Care, Inc.
Tulsa, Oklahoma 74146

MEDICATION Guide

Didanosine Delayed-Release Capsules (enteric-coated pellets)

Read this Medication Guide before you start taking didanosine delayed-release capsules and each time you get a refill. There may be new information. This information does not take the place of talking with your healthcare provider about your medical condition or your treatment. You and your healthcare provider should talk about your treatment with didanosine delayed-release capsules before you start taking it and at regular check-ups. You should stay under your healthcare provider’s care when taking didanosine delayed-release capsules.

What is the most important information I should know about Didanosine Delayed-Release Capsules?

Didanosine Delayed-Release Capsules may cause serious side effects, including:

1. Swelling of your pancreas (pancreatitis) that may cause death. Pancreatitis can happen at any time during your treatment with Didanosine Delayed-Release Capsules. Before you start taking didanosine delayed-release capsules, tell your healthcare provider if you:

- have had pancreatitis
- have advanced HIV (human immunodeficiency virus) infection
- have kidney problems
- drink alcoholic beverages
- take a medicine called ZERIT® (stavudine)

It is important to call your healthcare provider right away if you have:

- stomach pain
- swelling of your stomach
- nausea and vomiting
- fever

1. Build-up of acid in your blood (lactic acidosis). Lactic acidosis must be treated in the hospital as it may cause death. Before you start taking didanosine delayed-release capsules, tell your healthcare provider if you:

- have liver problems
- are pregnant. There have been deaths reported in pregnant women who get lactic acidosis after taking didanosine delayed-release capsules and ZERIT (stavudine).
- are overweight
- have been treated for a long time with other medicines to treat HIV

It is important to call your healthcare provider right away if you:

- feel weak or tired
- have unusual (not normal) muscle pain
- have trouble breathing
- have stomach pain with nausea and vomiting
- feel cold, especially in your arms and legs
- feel dizzy or light-headed
- have a fast or irregular heartbeat

1. Liver problems. Serious liver problems have happened in some people (including pregnant women) who take didanosine delayed-release capsules. These problems include liver enlargement (hepatomegaly), fat in the liver (steatosis), liver failure, and high blood pressure in the large vein of the liver (portal hypertension). Severe liver problems can lead to liver transplantation or death in some people taking didanosine delayed-release capsules. Your healthcare provider should check your liver function while you are taking didanosine delayed-release capsules. You should be especially careful if you have a history of heavy alcohol use or liver problems.

It is important to call your healthcare provider right away if you have:

-
  -
    - yellowing of your skin or the white of your eyes (jaundice)
    - dark urine
    - pain on the right side of your stomach
    - swelling of your stomach
    - easy bruising or bleeding
    - loss of appetite
    - nausea or vomiting
    - vomiting blood or dark colored stools (bowel movements)

What is Didanosine Delayed-Release Capsules?

Didanosine delayed-release capsules are a prescription medicine used with other antiretroviral medicines to treat human immunodeficiency virus (HIV) infection in children and adults. Didanosine delayed-release capsule belongs to a class of drugs called nucleoside analogues.

Didanosine delayed-release capsules will not cure your HIV infection. At present there is no cure for HIV infection. Even while taking didanosine delayed-release capsules, you may continue to have HIV-related illnesses, including infections with other disease-producing organisms. Continue to see your healthcare provider regularly and report any medical problems that occur.

Who should not take Didanosine Delayed-Release Capsules?

Do not take Didanosine Delayed-Release Capsules if you take:

• ZYLOPRIM®, LOPURIN®, ALOPRIM® (allopurinol)

• COPEGUS®, REBETOL®, RIBASPHERE®, RIBAVIRIN®, VIRAZOLE® (ribavirin)

What should I tell my healthcare provider before taking Didanosine Delayed-Release Capsules?

Before you take didanosine delayed-release capsules, tell your healthcare provider if you:

- have or had kidney problems
- have or had liver problems (such as hepatitis)
- have or had persistent numbness, tingling, or pain in the hands or feet (neuropathy)
- have any other medical conditions
- are pregnant or plan to become pregnant. It is not known if didanosine delayed-release capsules will harm your unborn baby. Tell your healthcare provider right away if you become pregnant while taking didanosine delayed-release capsules. You and your healthcare provider will decide if you should take didanosine delayed-release capsules while you are pregnant.

Pregnancy Registry: There is a pregnancy registry for women who take antiviral medicines during pregnancy. The purpose of the registry is to collect information about the health of you and your baby. Talk to your doctor about how you can take part in this registry.

- arebreastfeeding or plan to breastfeed. Do not breastfeed. It is not known if didanosine delayed-release capsules can be passed to your baby in your breast milk and whether it could harm your baby. Also, mothers with HIV-1 should not breastfeed because HIV-1 can be passed to the baby in the breast milk.

Tell your healthcare provider about all the medicines you take, including prescription and non-prescription medicines, vitamins and herbal supplements. Didanosine delayed-release capsules may affect the way other medicines work, and other medicines may affect how didanosine delayed-release capsules works.

Especially tell your healthcare provider if you take:

- CYTOVENE®, VALCYTE® (ganciclovir)
- DOLOPHINE® HYDROCHLORIDE, METHADOSE® (methadone)
- VIRACEPT® (nelfinavir)
- VIREAD® (tenofovir disoproxil fumarate)
- alcoholic beverages

Know the medicines you take. Keep a list of your medicines and show it to your healthcare provider and pharmacist when you get a new medicine.

Ask your healthcare provider if you are not sure if you take one of the medicines listed above.

How should I take Didanosine Delayed-Release Capsules?

- Take didanosine delayed-release capsules exactly as your healthcare provider tells you to take it.
- Your healthcare provider will tell you how much didanosine delayed-release capsules to take and when to take it.
- Your healthcare provider may change your dose. Do not change your dose of didanosine delayed-release capsules without talking to your healthcare provider.
- Do not take Didanosine Delayed-Release Capsuleswith food. Take didanosine delayed-release capsules on an empty stomach.
- Take didanosine delayed-release capsules whole. Do not break, crush, dissolve, or chew didanosine delayed-release capsules before swallowing. If you cannot swallow didanosine delayed-release capsules whole, tell your healthcare provider. You may need a different medicine.
- Try not to miss a dose, but if you do, take it as soon as possible. If it is almost time for the next dose, skip the missed dose and continue your regular dosing schedule.
- Some medicines should not be taken at the same time of day that you take Didanosine Delayed-Release Capsules. Check with your healthcare provider.
- If your kidneys are not working well, your healthcare provider will need to do regular blood and urine tests to check how they are working while you take didanosine delayed-release capsule. Your healthcare provider may also lower your dosage of didanosine delayed-release capsule if your kidneys are not working well.
- If you take too much Didanosine Delayed-Release Capsules, contact a poison control center or emergency room right away.

What should I avoid while taking Didanosine Delayed-Release Capsules?

- Alcohol. Do not drink alcohol while taking didanosine delayed-release capsules. Alcohol may increase your risk of getting pain and swelling of your pancreas (pancreatitis) or may damage your liver.

What are the possible side effects of Didanosine Delayed-Release Capsules?

Didanosine delayed-release capsules can cause pancreatitis, lactic acidosis, and liver problems. See “What is the most important information I should know about didanosine delayed-release capsules?” at the beginning of this Medication Guide.

- Vision changes. You should have regular eye exams while taking didanosine delayed-release capsules.
- Peripheral neuropathy. Symptoms include: numbness, tingling, or pain in your hands or feet. This condition is more likely to happen in people who have had it before, in patients taking medicines that affect the nerves, and in people with advanced HIV disease. A child may not notice these symptoms. Ask the child’s healthcare provider for the signs and symptoms of peripheral neuropathy in children.
- Changes in your immune system (immune reconstitution syndrome). Your immune system may get stronger and begin to fight infections that have been hidden in your body for a long time. Tell your healthcare provider if you start having new or worse symptoms of infection after you start taking HIV medicine.
- Changes in body fat (fat redistribution). Changes in body fat have been seen in people who take antiretroviral medicines. These changes may include:
- more fat in or around your

− upper back and neck (buffalo hump)

− breasts or chest

− trunk

- less fat in your

− legs

− arms

− face

Tell your healthcare provider if you have any of the symptoms listed above.

The most common side effects of didanosine delayed-release capsules include:

- diarrhea
- stomach pain
- nausea
- vomiting
- headache
- rash

Tell your healthcare provider if you have any side effect that bothers you or that does not go away.

These are not all the possible side effects of didanosine delayed-release capsules. For more information, ask your healthcare provider or pharmacist.

Call your doctor for medical advice about side effects. You may report side effects to FDA at 1-800-FDA-1088.

How should I store Didanosine Delayed Release Capsules?

- Store didanosine delayed-release capsules at 20o to 25o C (68o to 77o F)
- Safely throw away any unused didanosine delayed-release capsules

Keep Didanosine Delayed-Release Capsulesand all medicines out of the reach of children and pets.

General Information about the safe and effective use of Didanosine Delayed-Release Capsules.

Avoid doing things that can spread HIV-1 infection to others.

- Do not share needles or other injection equipment.
- Do not share personal items that can have blood or body fluids on them, like toothbrushes and razor blades.
- Do not have any kind of sex without protection. Always practice safe sex by using a latex or polyurethane condom or other barrier method to lower the chance of sexual contact with semen, vaginal secretions, or blood.

Medicines are sometimes prescribed for purposes other than those listed in a Medication Guide. Do not use didanosine delayed-release capsules for a condition for which it was not prescribed. Do not give didanosine delayed-release capsules to other people, even if they have the same symptoms as you have. It may harm them.

Do not keep medicine that is out of date or that you no longer need. Dispose of unused medicines through community take-back disposal programs when available or place didanosine delayed-release capsules in an unrecognizable closed container in the household trash.

This Medication Guide summarizes the most important information about didanosine delayed-release capsules. If you would like more information about didanosine delayed-release capsules, talk with your healthcare provider. You can ask your healthcare provider or pharmacist for information about didanosine delayed-release capsules that is written for health professionals. For more information call 1-888-838-2872, Medical Affairs.

What are the ingredients in Didanosine Delayed-Release Capsules?

Active Ingredients: didanosine

Inactive Ingredients:

Black iron oxide, croscarmellose sodium, D&C yellow no. 10 aluminum lake, FD&C blue no. 1, FD&C blue no. 1 aluminum lake, FD&C blue no. 2 aluminum lake, FD&C red no. 40 aluminum lake, gelatin, hydroxypropyl cellulose, hypromellose, methacrylic acid copolymer dispersion, microcrystalline cellulose, polydextrose, polyethylene glycol, propylene glycol, shellac glaze, silicon dioxide, sodium hydroxide, talc, titanium dioxide, triacetin and triethyl citrate. The 200 mg and 400 mg capsule also contains D&C red no. 33 and FD&C yellow no. 6, and the 250 mg also contains D&C red no. 28.

ZERIT® is a registered trademark of Bristol-Myers Squibb Company.

LOPURIN® is a registered trademark of Dr. Reddy’s Labs.

ALOPRIM® is a registered trademark of Bioniche Pharma.

COPEGUS®, CYTOVENE®, and VALCYTE® are registered trademarks of Hoffman-La Roche.

REBETOL® is a registered trademark of Schering Corporation.

RIBASPHERE® is a registered trademark of Three Rivers Pharms.

VIRAZOLE® is a registered trademark of Valeant Pharm.

DOLOPHINE® is a registered trademark of Roxane Labs.

METHADOSE® is a registered trademark of Mallinckrodt, Inc.

VIRACEPT® is a registered trademark of Aguoron Pharmaceuticals, Inc.

VIREAD® is a registered trademark of Gilead Sciences, Inc.

TEVA PHARMACEUTICALS USA
Sellersville, PA 18960

Rev. D 12/2011

This Medication Guide has been approved by the U.S. Food and Drug Administration.

PRINCIPAL DISPLAY PANEL

Didanosine Delayed-Release Capsules 250 mg 30s Label Text

NDC 54868-5464-1

DIDANOSINE
Delayed-Release
Capsules (enteric-coated pellets)

250 mg

PHARMACIST: Dispense the accompanying
Medication Guide to each patient.

Rx only

30 CAPSULES (Unit-of-Use)